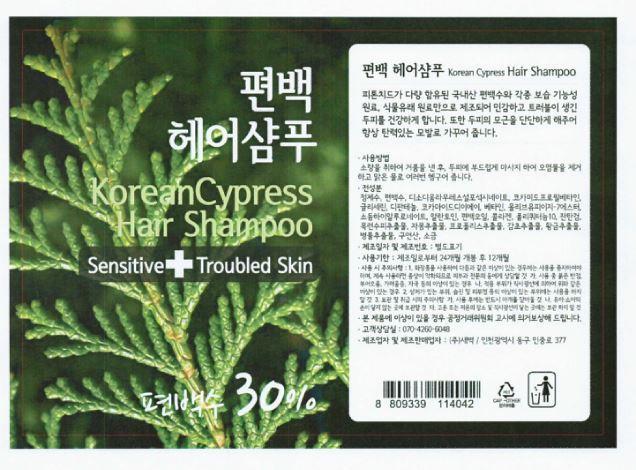 DRUG LABEL: KOREAN CYPRESS HAIR
NDC: 69602-2001 | Form: SHAMPOO
Manufacturer: Saebyuck Corp.
Category: otc | Type: HUMAN OTC DRUG LABEL
Date: 20150308

ACTIVE INGREDIENTS: GLYCERIN 4 g/100 mL
INACTIVE INGREDIENTS: WATER; DEXPANTHENOL; CARBOXYMETHYLCELLULOSE SODIUM

Drug Facts

ACTIVE INGREDIENT

glycerine

INACTIVE INGREDIENT

water, d-panthenol, allantoin, collagen, cellulose gum, grapefruit fruit ext. propolis ext, etc

PURPOSE

skin protectant

keep out of reach of the children

INDICATIONS AND USAGE

put a small amount of shampoo onto the plam of your hand
massage the shampoo smothly into the scalp with your fingertips and rinse all of the shampoo out with warm water

WARNINGS

・Stop using the product when you have skin problems or the product disagrees with your skin
・Stop using the product immediately and consult a dermatologist if you have redness, swelling, itching or irritation on the skin while or after using the product.
・Don't place the product in any place where it will be subjected to extremely high or low temperatures or direct sunlight.

DOSAGE AND ADMINISTRATION

for external use only